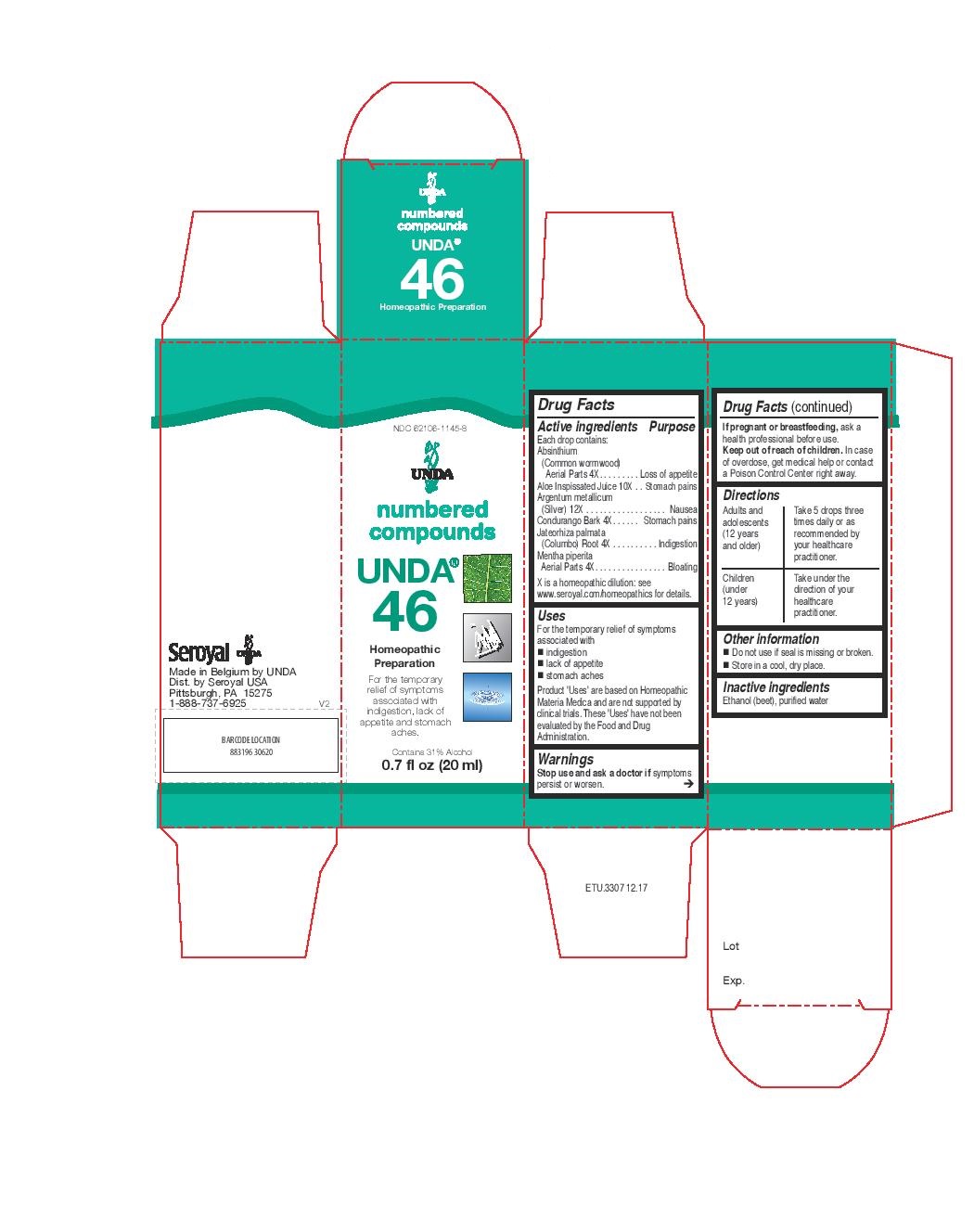 DRUG LABEL: Unda 46
NDC: 62106-1145 | Form: LIQUID
Manufacturer: Seroyal USA
Category: homeopathic | Type: HUMAN OTC DRUG LABEL
Date: 20221109

ACTIVE INGREDIENTS: ALOE 10 [hp_X]/20 mL; SILVER 12 [hp_X]/20 mL; WORMWOOD 4 [hp_X]/20 mL; JATEORHIZA CALUMBA ROOT 4 [hp_X]/20 mL; MARSDENIA CONDURANGO BARK 4 [hp_X]/20 mL; MENTHA PIPERITA 4 [hp_X]/20 mL
INACTIVE INGREDIENTS: ALCOHOL; WATER

Unda 46

Active ingredients
Each drop contains:
Absinthium (Common wormwood) Aerial Parts 4X
Aloe Inspissated Juice 10X
Argentum metallicum (Silver) 12X
Condurango Bark 4X
Jateorhiza palmata (Columbo) Root 4X
Mentha piperita Aerial Parts 4X

Uses
For the temporary relief of symptoms associated with
indigestion
lack of appetite
stomach aches

Warnings
Stop use and ask a doctor if symptoms persist or worsen.Warnings

If pregnant or breastfeeding, ask a health professional before use.

Keep out of reach of children.

In case of overdose, get medical help or contact a
Poison Control Center right away.

PREGNANCY OR BREAST FEEDING

If pregnant or breastfeeding, ask a health professional before use.

Keep out of reach of children.

OVERDOSAGE

In case of overdose, get medical help or contact a

Poison Control Center right away.

Stop use and ask a doctor if symptoms persist or worsen.

Inactive ingredients
Ethanol (beet), purified water

Other information
Do not use if seal is missing or broken.
Store in a cool, dry place.

Directions
Adults and adolescents (12 years and older)

Take 5 drops three times daily or as recommended by your healthcare practitioner.

Children (under 12 years)

Take under the direction of your healthcare practitioner.

Uses
For the temporary relief of symptoms associated with
indigestion
lack of appetite
stomach aches

Directions
Adults and adolescents (12 years and older)

Take 5 drops three times daily or as recommended by your healthcare practitioner.

Children (under 12 years)

Take under the direction of your healthcare practitioner.

PACKAGE LABEL

NDC 62106-1145-8

UNDA

numbered compounds

UNDA 46

Homeopathic Preparation

For the temporary relief of symptoms
associated with indigestion, lack of
appetite and stomach aches.

Contains 31% Alcohol
0.7 fl oz (20 ml)